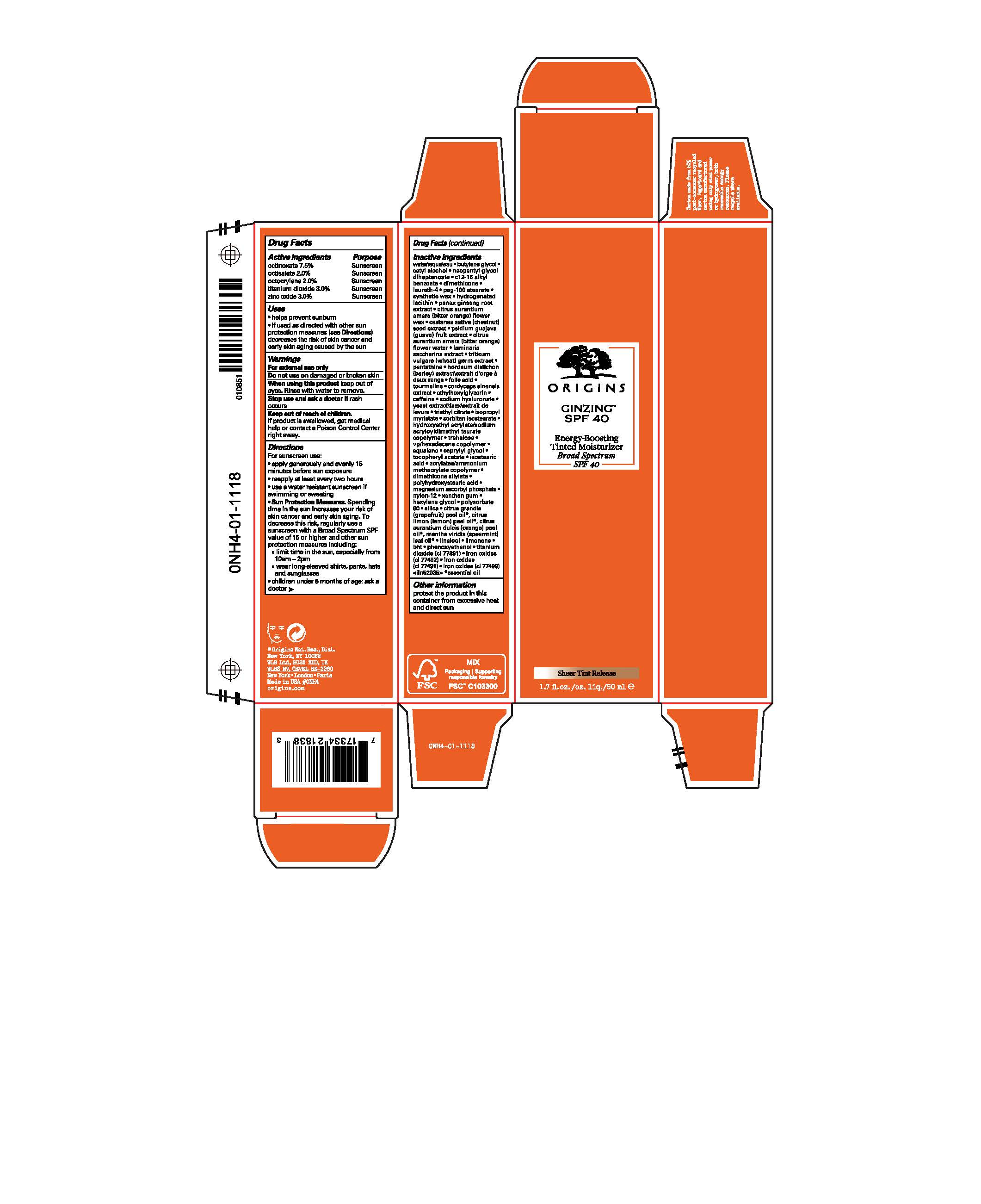 DRUG LABEL: ORIGINS GINZING ENERGY-BOOSTING TINTED MOISTURIZER BROAD SPECTRUM SPF 40
NDC: 59427-016 | Form: LIQUID
Manufacturer: ORIGINS NATURAL RESOURCES INC.
Category: otc | Type: HUMAN OTC DRUG LABEL
Date: 20241225

ACTIVE INGREDIENTS: OCTINOXATE 75 mg/1 mL; OCTISALATE 20 mg/1 mL; OCTOCRYLENE 20 mg/1 mL; TITANIUM DIOXIDE 30 mg/1 mL; ZINC OXIDE 30 mg/1 mL
INACTIVE INGREDIENTS: BARLEY; TRIETHYL CITRATE; VINYLPYRROLIDONE/HEXADECENE COPOLYMER; NEOPENTYL GLYCOL DIHEPTANOATE; SYNTHETIC BEESWAX; AMMONIUM ACRYLOYL DIMETHYLTAURATE/METHACRYLATE, DIMETHYLACRYLAMIDE AND METHACRYLIC ACID COPOLYMER, PPG-3 GLYCERYL TRIACRYLATE CROSSLINKED (100000 MW); WATER; BUTYLENE GLYCOL; CETYL ALCOHOL; ALKYL (C12-15) BENZOATE; DIMETHICONE; LAURETH-4; PEG-100 STEARATE; HYDROGENATED SOYBEAN LECITHIN; LEMON OIL, COLD PRESSED; CITRUS MAXIMA FRUIT RIND OIL; SPEARMINT OIL; ORANGE OIL, COLD PRESSED; LIMONENE, (+)-; LINALOOL, (+)-; PANAX GINSENG ROOT OIL; CITRUS AURANTIUM FLOWER WAX; SPANISH CHESTNUT; GUAVA; CITRUS AURANTIUM FLOWER OIL; SACCHARINA LATISSIMA; WHEAT GERM; PANTETHINE; ALV-001; FOLIC ACID; SCHORL TOURMALINE; OPHIOCORDYCEPS SINENSIS; ETHYLHEXYLGLYCERIN; CAFFEINE; HYALURONATE SODIUM; ISOPROPYL MYRISTATE; HYDROXYETHYL ACRYLATE/SODIUM ACRYLOYLDIMETHYL TAURATE COPOLYMER (100000 MPA.S AT 1.5%); TREHALOSE; AMMONIO METHACRYLATE COPOLYMER TYPE A; SQUALANE; CAPRYLYL GLYCOL; .ALPHA.-TOCOPHEROL ACETATE; YEAST, UNSPECIFIED; ISOSTEARIC ACID; SILICA DIMETHYL SILYLATE; POLYHYDROXYSTEARIC ACID (2300 MW); MAGNESIUM ASCORBYL PHOSPHATE; NYLON-12; XANTHAN GUM; HEXYLENE GLYCOL; POLYSORBATE 60; SILICA, TRIMETHYLSILYL CAPPED; BUTYLATED HYDROXYTOLUENE; PHENOXYETHANOL; FERRIC OXIDE RED; FERRIC OXIDE YELLOW; FERROSOFERRIC OXIDE; SORBITAN ISOSTEARATE

ORIGINS GINZING™ ENERGY-BOOSTING TINTED MOISTURIZER BROAD SPECTRUM SPF 40

Drug Facts

ACTIVE INGREDIENT

Active ingredients | Purpose
octinoxate 7.5% | Sunscreen
octisalate 2.0% | Sunscreen
octocrylene 2.0% | Sunscreen
titanium dioxide 3.0% | Sunscreen
zinc oxide 3.0% | Sunscreen

Uses

- helps prevent sunburn
- if used as directed with other sun protection measures (see Directions) decreases the risk of skin cancer and early skin aging caused by the sun

Warnings

For external use only

Do not use on damaged or broken skin

When using this product keep out of eyes. Rinse with water to remove.

Stop use and ask a doctor if rash occurs

Keep out of reach of children.

If product is swallowed, get medical help or contact a Poison Control Center right away.

Directions

For sunscreen use:

- apply generously and evenly 15 minutes before sun exposure
- reapply at least every two hours
- use a water resistant sunscreen if swimming or sweating
- Sun Protection Measures. Spending time in the sun increases your risk of skin cancer and early skin aging. To decrease this risk, regularly use a sunscreen with a Broad Spectrum SPF value of 15 or higher and other sun protection measures including:
  - limit time in the sun, especially from 10am – 2pm
  - wear long-sleeved shirts, pants, hats and sunglasses
- children under 6 months of age: ask a doctor

Inactive ingredients

water\aqualeau • butylene glycol• cetyl alcohol • neopentyl glycol diheptanoate • c12-15 alkyl benzoate • dimethicone • laureth-4 • peg-100 stearate • synthetic wax• hydrogenated lecithin• panax ginseng root extract• citrus aurantium amara (bitter orange) flower wax• castanea sativa (chestnut) seed extract• psidium guajava (guava) fruit extract • citrus aurantium amara (bitter orange) flower water• laminaria saccharina extract• triticum vulgare (wheat) germ extract• pantethine • hordeum distichon (barley) extract\extrait d'orge a deux rangs • folic acid• tourmaline• cordyceps sinensis extract• ethylhexylglycerin • caffeine• sodium hyaluronate • yeast extract\faex\extrait de levure • triethyl citrate• isopropyl myristate • sorbitan isostearate • hydroxyethyl acrylate/sodium acryloyldimethyl taurate copolymer • trehalose • vp/hexadecene copolymer• squalane • caprylyl glycol• tocopheryl acetate • isostearic acid• acrylates/ammonium methacrylate copolymer• dimethicone silylate • polyhydroxystearic acid • magnesium ascorbyl phosphate• nylon-12 • xanthan gum• hexylene glycol • polysorbate 60 •silica• citrus grandis (grapefruit) peel oil*, citrus limon (lemon) peel oil*, citrus aurantium dulcis (orange) peel oil*, mentha viridis (spearmint) leaf oil*• linalool • limonene • bht • phenoxyethanol • titanium dioxide (ci 77891) • iron oxides (ci 77492) • iron oxides (ci 77491) • iron oxides (ci 77499) <iln52035> *essential oil

Other information

protect the product in this container from excessive heat and direct sun

PRINCIPAL DISPLAY PANEL - 50 ml Tube Carton

ORIGINS

GINZING™
SPF 40

Energy-Boosting
Tinted Moisturizer
Broad Spectrum
SPF 40

Sheer Tint Release

1.7 fl.oz./oz. liq./50 ml e